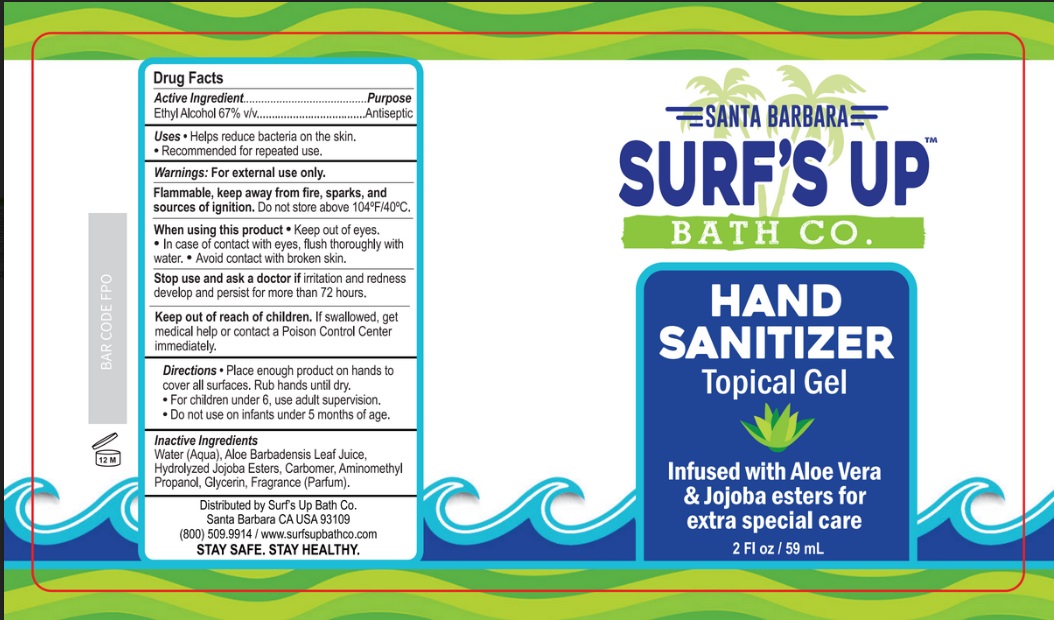 DRUG LABEL: Surfs Up Bath Co. Hand Sanitizer
NDC: 90050-001 | Form: LIQUID
Manufacturer: The Little Bath Co. LLC
Category: otc | Type: HUMAN OTC DRUG LABEL
Date: 20200718

ACTIVE INGREDIENTS: ALCOHOL 67 mL/100 mL
INACTIVE INGREDIENTS: WATER; ALOE VERA LEAF; HYDROLYZED JOJOBA ESTERS (POTASSIUM SALTS); CARBOMER HOMOPOLYMER TYPE C (ALLYL PENTAERYTHRITOL CROSSLINKED); AMINOMETHYLPROPANOL; GLYCERIN; FRAGRANCE LAVENDER & CHIA F-153480

Active Ingredient

Ethyl Alcohol 67% v/v.

Purpose

Antiseptic

Use

- Helps reduce bacteria on the skin.
- Recommended for repeated use.

Warnings

For external use only.

Flammable, keep away from fire, sparks, and sources of ignition. Do not store above 104°F/40°C.

When using this product Keep out of eyes. In case of contact with eyes, flush thoroughly with water. Avoid contact with broken skin.

Stop use and ask a doctor if irritation and redness develop and persist for more than 72 hours.

Keep out of reach of children. If swallowed, get medical help or contact a Poison Control Center right away.

Directions

- Place enough product on hands to cover all surfaces. Rub hands together until dry.
- For children under 6, use adult supervision.
- Do not use on infants under 5 months of age.

Inactive ingredients

Water (Aqua), Aloe Barbadensis Leaf Juice, Hydrolyzed Jojoba Esters, Carbomer, Aminomethyl Propanol, Glycerin, Fragrance (Parfum).